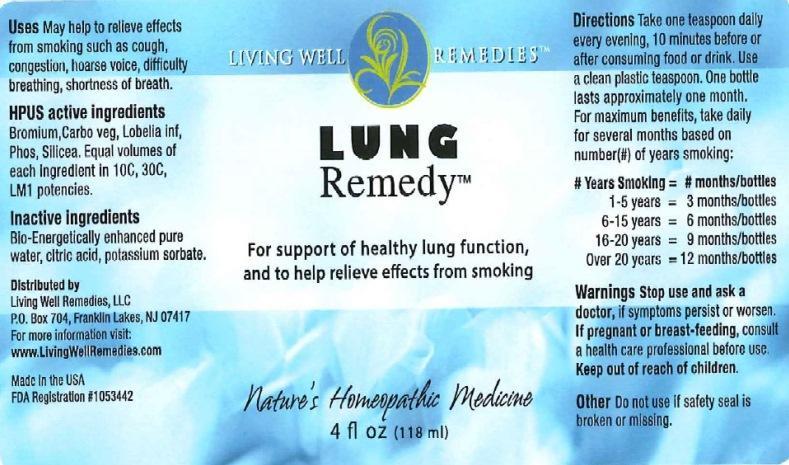 DRUG LABEL: Lung Remedy
NDC: 53852-0011 | Form: LIQUID
Manufacturer: Living Well Remedies, LLC
Category: homeopathic | Type: HUMAN OTC DRUG LABEL
Date: 20170508

ACTIVE INGREDIENTS: BROMINE 10 [hp_C]/118 mL; ACTIVATED CHARCOAL 10 [hp_C]/118 mL; LOBELIA INFLATA 10 [hp_C]/118 mL; PHOSPHORUS 10 [hp_C]/118 mL; SILICON DIOXIDE 10 [hp_C]/118 mL
INACTIVE INGREDIENTS: WATER; ANHYDROUS CITRIC ACID; POTASSIUM SORBATE

Lung Remedy

ACTIVE INGREDIENT

Active Ingredients: Official HPUS: Bromium, Carbo vegetabilis, Lobelia inflata, Phosphorus, Silicea. Equal volumes of each ingredient in 10C, 30C, LM1 potency.

INACTIVE INGREDIENT

Inactive ingredients: Bio-Energetically enhanced pure water, citric acid and potassium sorbate.

INDICATIONS AND USAGE

Indications: May help to relieve effects from smoking such as cough, congestion, hoarse voice, difficulty breathing, shortness of breath.

WARNINGS

Warnings: Stop use and ask a doctor, if symptoms persist or worsen. If pregnant or breast-feeding, consult a health care professional before use.

Keep out of reach of children.

Do not use if safety seal is broken or missing.

Directions:

Take one teaspoon daily every evening, 10 minutes away from food or drink. Use a clean plastic teaspoon. One bottle lasts approximately one month. For maximum benefits, take daily for several months based on number (#) of years smoking:

Years Smoking = # months/bottles

1-5 years = 3 months/bottles

6-15 years = 6 months/bottles

16-20 years = 9 months/bottles

Over 20 years = 12 months/bottles

PURPOSE

May help to relieve effects from smoking such as:

- cough
- congestion
- hoarse voice
- difficulty breathing
- shortness of breath